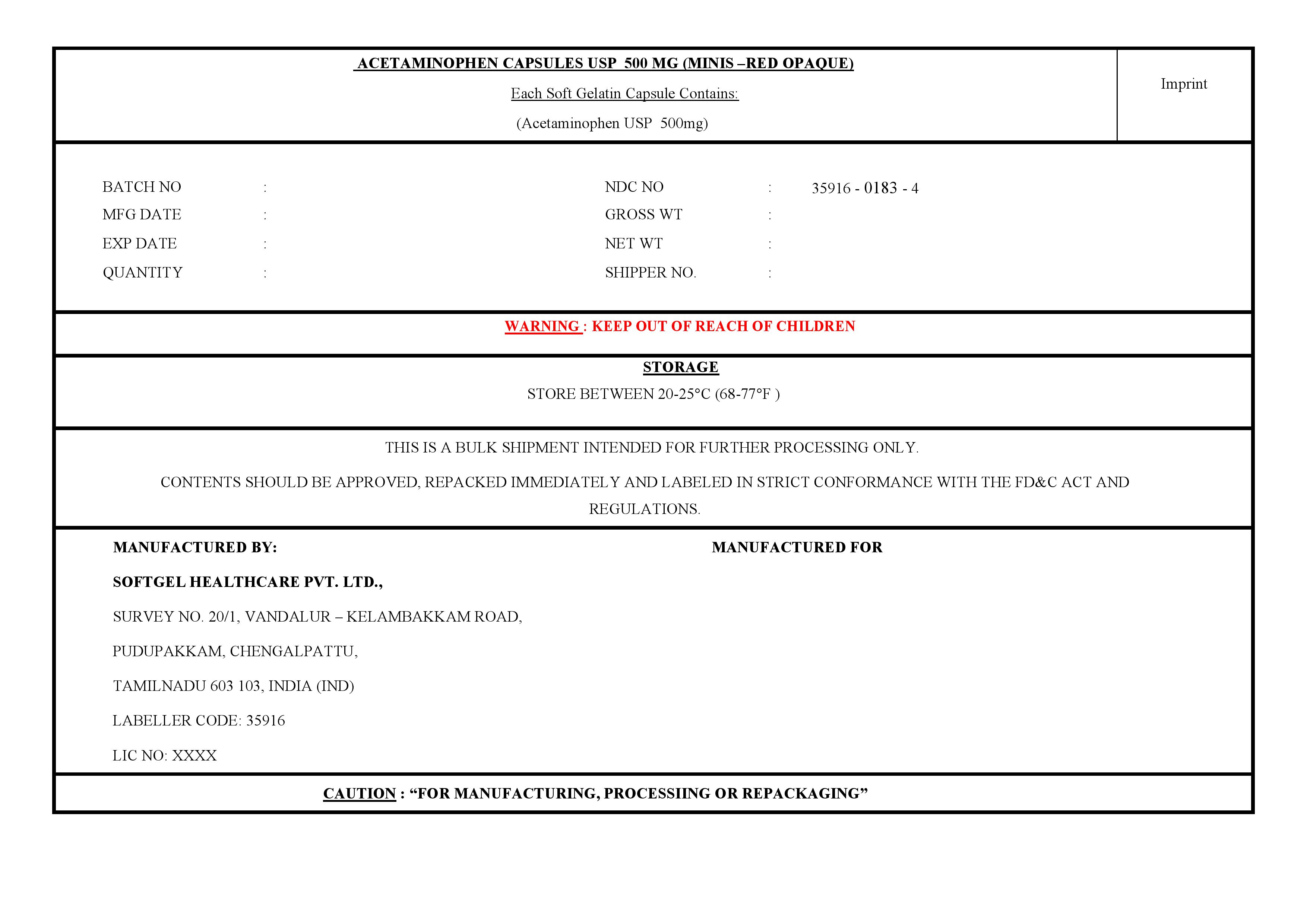 DRUG LABEL: Acetaminophen
NDC: 35916-0183 | Form: CAPSULE, LIQUID FILLED
Manufacturer: Softgel Healthcare Pvt Ltd
Category: otc | Type: HUMAN OTC DRUG LABEL
Date: 20260113

ACTIVE INGREDIENTS: ACETAMINOPHEN 500 mg/1 1
INACTIVE INGREDIENTS: GLYCERIN; SORBITOL; POLYETHYLENE GLYCOL 400; FD&C RED NO. 40; TITANIUM DIOXIDE; WATER; GELATIN; POVIDONE K30; POLYOXYL 40 HYDROGENATED CASTOR OIL

Acetaminophen Capsules USP 500mg (Minis - Red Opaque)

Active ingredient (in each Softgel)

Acetaminophen 500 mg

Purpose

Pain reliever/fever reducer

Uses

•Temporarily relieves minor aches and pains due to:

• the common cold • headache • backache • minor pain of arthritis • toothache • muscular aches • premenstrual and menstrual cramps • temporarily reduces fever

Warnings

Liver warning:This product contains acetaminophen.

Severe liver damage may occur if you take

- more than 4,000 mg of acetaminophen in 24 hours
- with other drugs containing acetaminophen
- 3 or more alcoholic drinks every day while using this product.

Allergy alert: acetaminophen may cause severe skin reactions.

symptoms may include:

- skin reddening
- blisters
- rash

If a skin reaction occurs, stop use and seek medical help right away.

Do not use

• with any other drug containing acetaminophen (prescription or nonprescription).

If you are not sure whether a drug contains acetaminophen, ask a doctor or pharmacist.

• if you are allergic to acetaminophen or any of the inactive ingredients in this product.

Ask a doctor before use if you have

• liver disease

Ask a doctor or pharmacist before use if you are

taking the blood thinning drug warfarin

Stop use and ask a doctor if

• pain gets worse or lasts more than 10 days

• fever gets worse or lasts more than 3 days

• new symptoms occur

• redness or swelling is present.

These could be signs of a serious condition.

If pregnant or breast-feeding,

ask a health professional before use.

Keep out of reach of children.

Overdose warnings:

In case of overdose, get medical help or contact a Poison Control Center right away. Quick medical attention is critical for adults as well as for children even if you do not notice any signs or symptoms.

Directions

• do not take more than directed (see overdose warning).

adults and children 12 years and over | • take 2 capsules every 6 hours while symptoms last; •do not take more than 6 capsules in 24 hours,unless directed by a doctor; • do not use for more than 10 days unless directed by a doctor
children under 12 years | ask a doctor

Other information

- store between 20-25°C (68-77°F)

Inactive ingredients

FD&C red 40, gelatin,glycerin, polyethylene glycol 400, polyoxyl 40 hydrogenated castor oil, povidone K30,purified water, sorbitol sorbitan solution, titanium dioxide